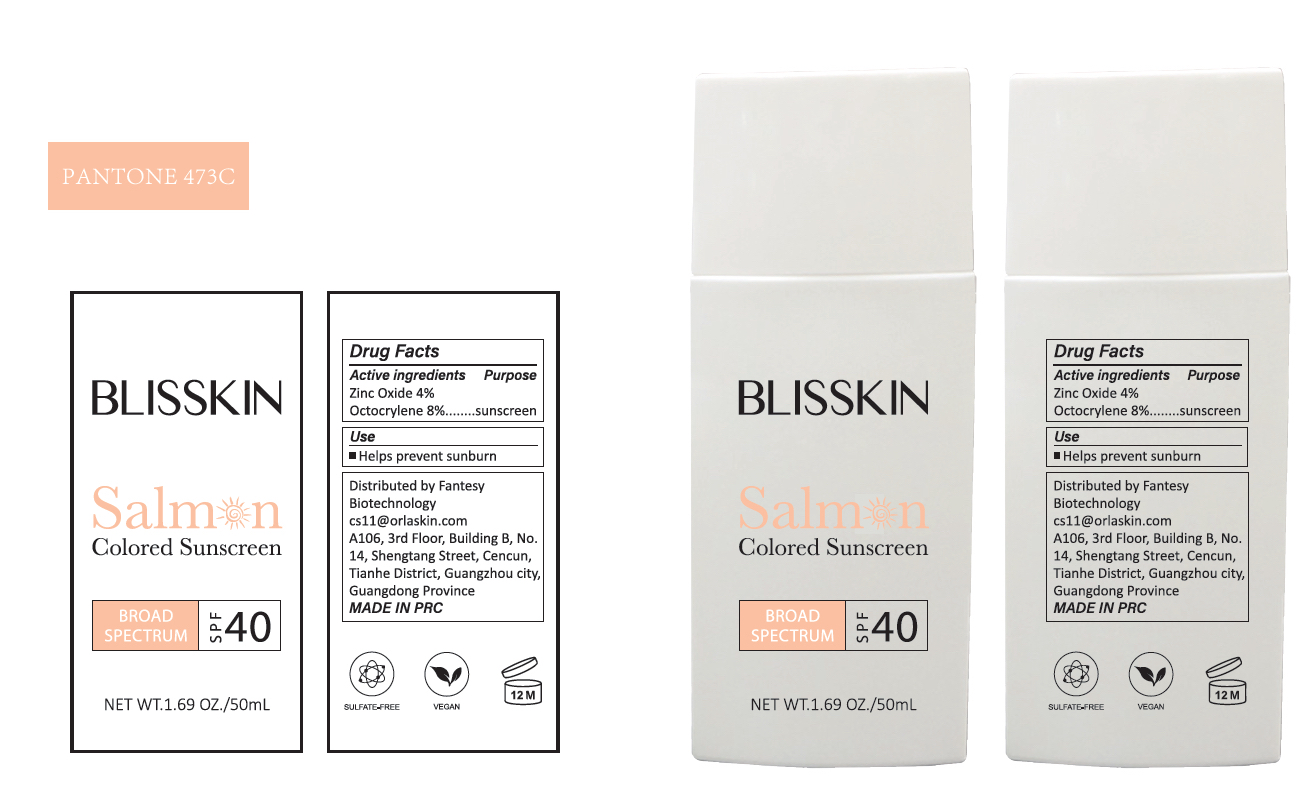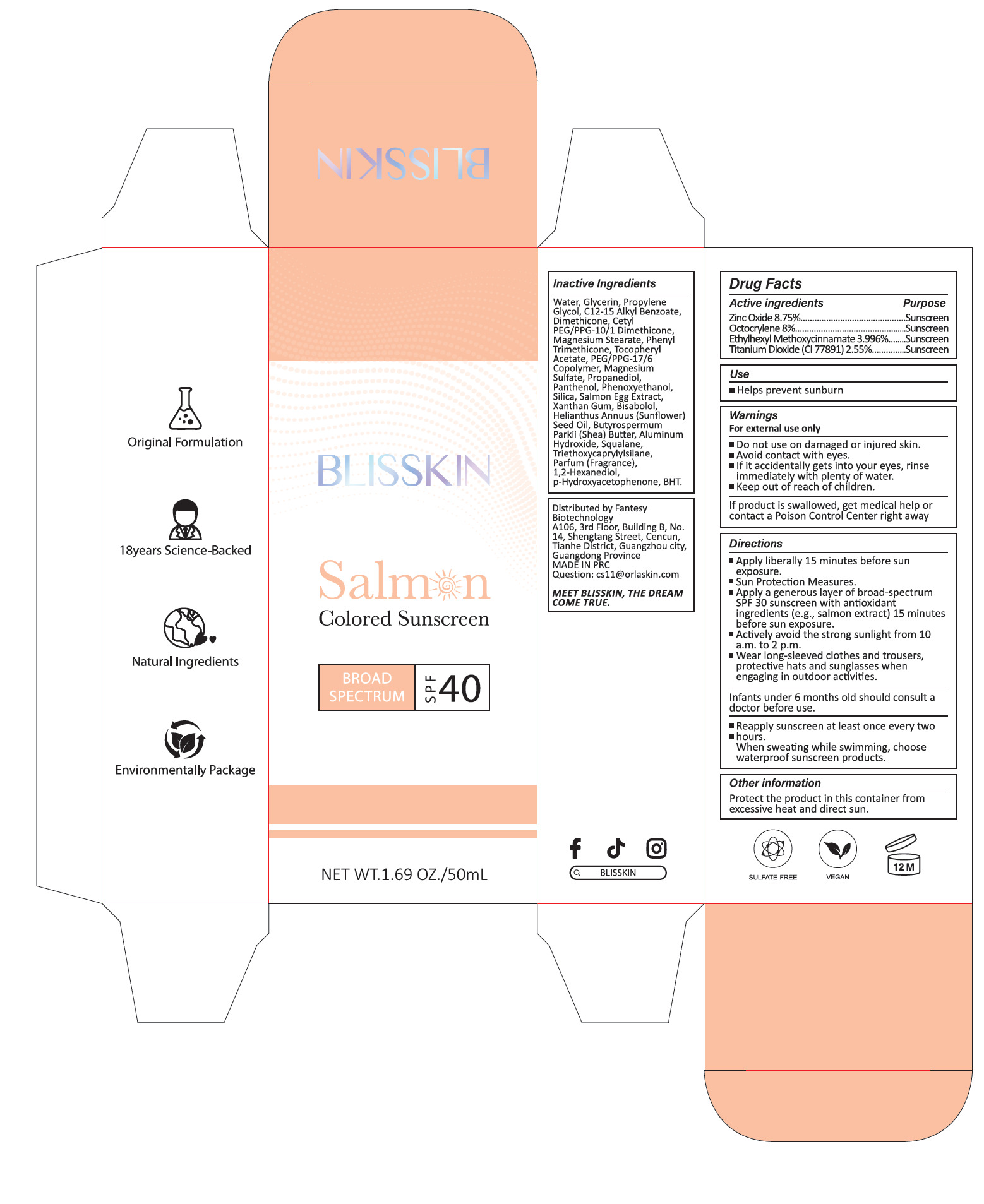 DRUG LABEL: salmon colored sunscreen
NDC: 83447-013 | Form: CREAM
Manufacturer: Guangzhou Fantesy Biotechnology Co.,Ltd
Category: otc | Type: HUMAN OTC DRUG LABEL
Date: 20251125

ACTIVE INGREDIENTS: ZINC OXIDE 8.75 g/100 mL; TITANIUM DIOXIDE 2.55 g/100 mL; ETHYLHEXYL METHOXYCINNAMATE 3.996 g/100 mL; OCTOCRYLENE 8 g/100 mL
INACTIVE INGREDIENTS: WATER; BISABOLOL; SALMON, UNSPECIFIED; HYDROXYACETOPHENONE; ALPHA-TOCOPHEROL ACETATE; GLYCERIN; HELIANTHUS ANNUUS (SUNFLOWER) SEED OIL; PEG/PPG-17/6 COPOLYMER; DIMETHICONE; 1,2-HEXANEDIOL; C12-15 ALKYL BENZOATE; BUTYROSPERMUM PARKII (SHEA) BUTTER; MAGNESIUM STEARATE; PROPYLENE GLYCOL; SILICA; SQUALANE; TRIETHOXYCAPRYLYLSILANE; XANTHAN GUM; CETYL PEG/PPG-10/1 DIMETHICONE (HLB 2); ALUMINUM HYDROXIDE; PHENYL TRIMETHICONE; MAGNESIUM SULFATE; PROPANEDIOL; PARFUMIDINE; PANTHENOL; PHENOXYETHANOL; BHT

83447-013

Active ingredients

Zinc Oxide 8.75%
Octocrylene 8%
Ethyhexyl Methoxycinnamate 3.996%.
Titanium Dioxide (CI 77891)2.55%

Purpose

Sunscreen

Uses

Helps prevent sunburn

Warnings

For external use only
■Do not use on damaged or injured skin.
■Avoid contact with eyes.
■If it accidentally gets into your eyes, rinse immediately with plenty of water.
■Keep out of reach of children.
If product is swallowed, get medical help or contact a Poison Control Center right away

Do not use on damaged or broken skin.

When using this product, keep out of eyes.

Stop use

Stop use and ask a doctor if rash occurs.

Keep out of reach of children

Directions

■Apply liberally 15 minutes before sun exposure.
■Sun Protection Measures.
■Apply a generous layer of broad-spectrum SPF 30 sunscreen with antioxidant ingredients (e.g., salmon extract) 15 minutes
before sun exposure.
■Actively avoid the strong sunlight from 10 a.m. to 2 p.m.
■Wear long-sleeved clothes and trousers, protective hats and sunglasses when engaging in outdoor activities.
Infants under 6 months old should consult a doctor before use.

■Reapply sunscreen at least once every two

■hours.

When sweating while swimming, choose waterproof sunscreen products.

Other information

Protect the product in this container from excessive heat and direct sun.

Inactive ingredients

Water, Glycerin, Propylene Glycol, C12-15 Alkyl Benzoate, Dimethicone, Cetyl
PEG/PPG-10/1 Dimethicone, Magnesium Stearate, PhenyI Trimethicone, TocopheryI
Acetate, PEG/PPG-17/6 Copolymer, Magnesium Sulfate, Propanediol, Panthenol, Phenoxyethanol,
Silica, Salmon Egg Extract, Xanthan Gum, Bisabolol, Helianthus Annuus (Sunflower)
Seed Oil, Butyrospermum Parkii (Shea) Butter, Aluminum Hydroxide, Squalane,
Triethoxycaprylylsilane, Parfum (Fragrance), 1,2-Hexanediol, p-Hydroxyacetophenone, BHT.